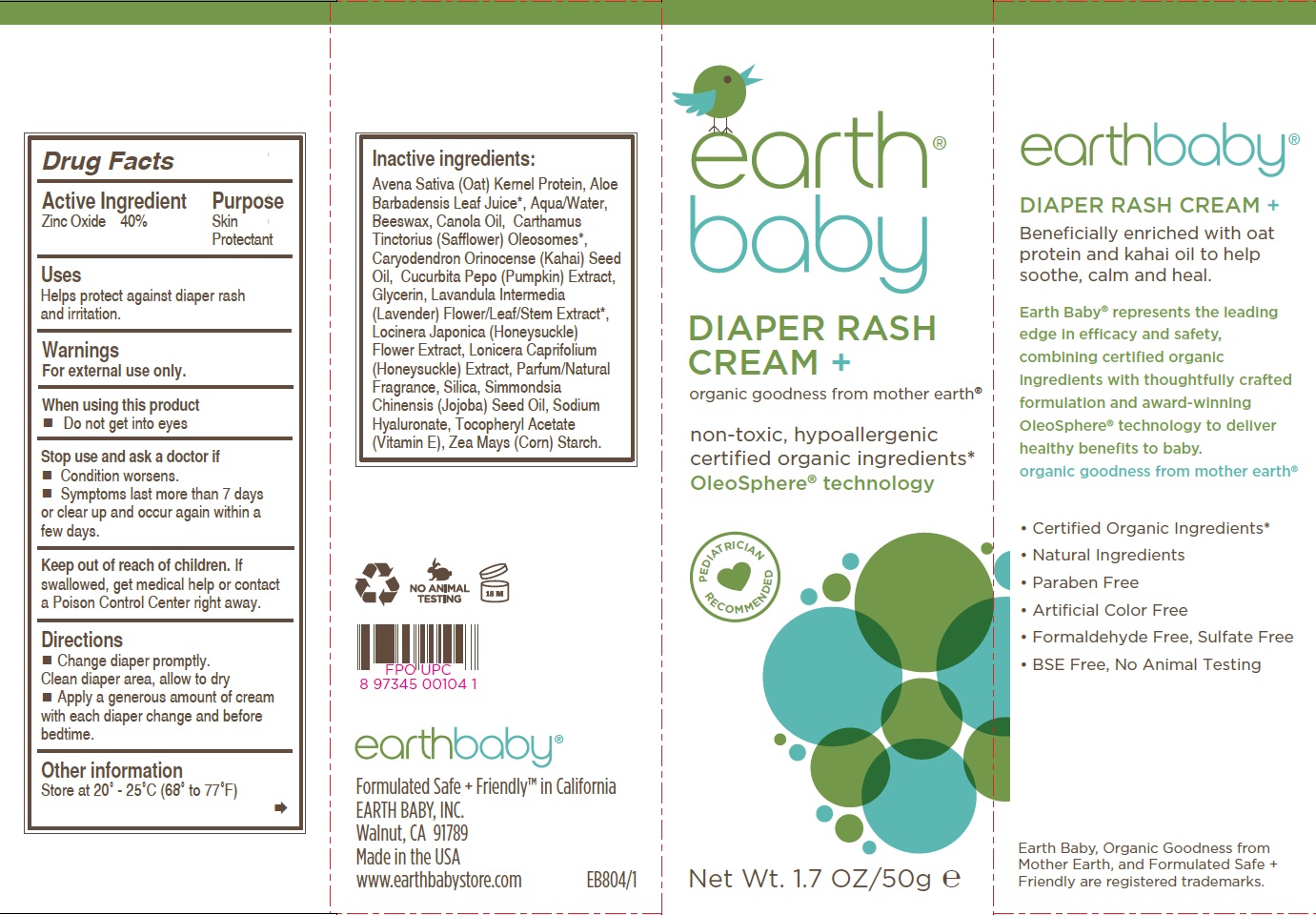 DRUG LABEL: Earth Baby Diaper Rash Cream
NDC: 62588-904 | Form: CREAM
Manufacturer: Earth Baby, Inc
Category: otc | Type: HUMAN OTC DRUG LABEL
Date: 20250506

ACTIVE INGREDIENTS: ZINC OXIDE 40 g/100 g
INACTIVE INGREDIENTS: ALOE; CARTHAMUS TINCTORIUS (SAFFLOWER) OLEOSOMES; CARYODENDRON ORINOCENSE WHOLE; CUCURBITA PEPO WHOLE; GLYCERIN; LAVANDULA X INTERMEDIA WHOLE; LONICERA CAPRIFOLIUM WHOLE; OAT KERNEL OIL; HYALURONATE SODIUM; LONICERA JAPONICA FLOWER; SILICON DIOXIDE; JOJOBA OIL; .ALPHA.-TOCOPHEROL ACETATE; WATER; CANOLA OIL

Earth Baby Diaper Rash Cream

Active Ingredient
Zinc Oxide 40%

PURPOSE

Skin Protectant

Warnings
For external use only.

When using this product Do not get into eyes

Stop use and ask a doctor if
Condition worsens.
Symptoms last more than 7 days or clear up and occur again within a few days.

Keep out of reach of children. If swallowed, get medical help or contact a Poison Control Center right away.

Directions
Change diaper promptly.
Clean diaper area, allow to dry
Apply a generous amount of creamwith each diaper change and before bedtime.

Other information
Store at 20° - 25°C (68° to 77°F)

Inactive ingredients:
Avena Sativa (Oat) Kernel Protein, Aloe Barbadensis Leaf Juice*, Aqua/Water, Beeswax, Canola Oil, Carthamus Tinctorius (Safflower) Oleosomes*, Caryodendron Orinocense (Kahai) Seed Oil, Cucurbita Pepo (Pumpkin) Extract, Glycerin, Lavandula Intermedia (Lavender) Flower/Leaf/Stem Extract*, Locinera Japonica (Honeysuckle) Flower Extract, Lonicera Caprifolium (Honeysuckle) Extract, Parfum/Natural Fragrance, Silica, Simmondsia Chinensis (Jojoba) Seed Oil, Sodium Hyaluronate, Tocopheryl Acetate (Vitamin E), Zea Mays (Corn) Starch.

INDICATIONS AND USAGE

Helps protect against diaper rash and irritation.